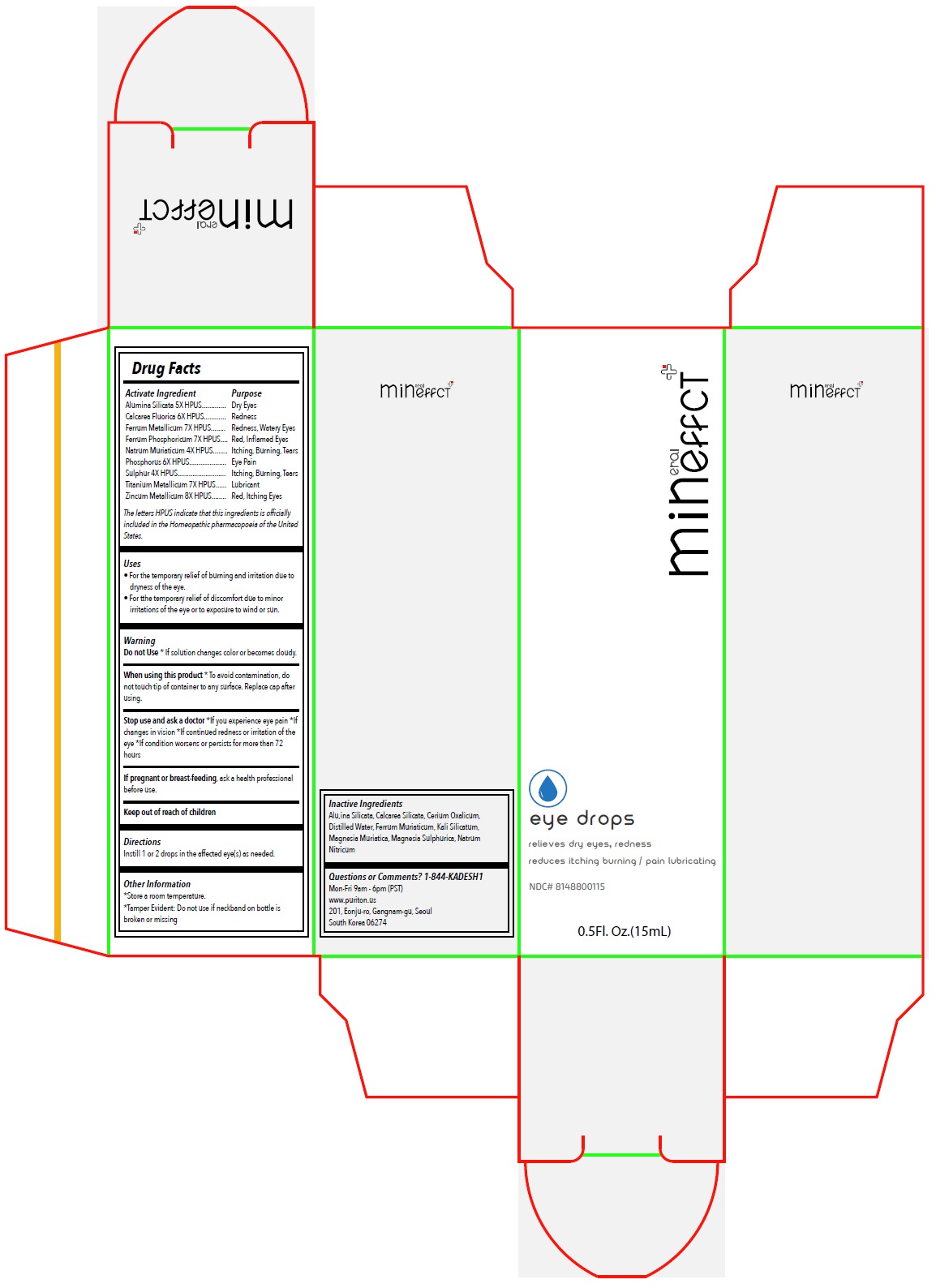 DRUG LABEL: Mineffect eye drops
NDC: 81488-001 | Form: SOLUTION/ DROPS
Manufacturer: Kadesh Incoporation Co,Ltd
Category: homeopathic | Type: HUMAN OTC DRUG LABEL
Date: 20240426

ACTIVE INGREDIENTS: KAOLIN 5 [hp_X]/15 mL; CALCIUM FLUORIDE 6 [hp_X]/15 mL; IRON 7 [hp_X]/15 mL; FERROSOFERRIC PHOSPHATE 7 [hp_X]/15 mL; SODIUM CHLORIDE 4 [hp_X]/15 mL; PHOSPHORUS 6 [hp_X]/15 mL; SULFUR 4 [hp_X]/15 mL; TITANIUM 7 [hp_X]/15 mL; ZINC 8 [hp_X]/15 mL
INACTIVE INGREDIENTS: CALCIUM SILICATE; CEROUS OXALATE NONAHYDRATE; WATER; FERRIC CHLORIDE HEXAHYDRATE; POTASSIUM SILICATE; MAGNESIUM CHLORIDE; MAGNESIUM SULFATE HEPTAHYDRATE; SODIUM NITRATE

Mineffect eye drops

Activate Ingredient

Alumina Silicata 5X HPUS
Calcarea Fluorica 6X HPUS
Ferrum Metallicum 7X HPUS
Ferrum Phosphoricum 7X HPUS
Natrum Muriaticum 4X HPUS
Phosphorus 6X HPUS
Sulphur 4X HPUS
Titanium Metallicum 7X HPUS
Zincum Metallicum 8X HPUS

The letters HPUS indicate that this ingredients is officially included in the Homeopathic pharmacopoeia of the United States.

Purpose

Dry Eyes
Redness
Redness, Watery Eyes
Red, Inflamed Eyes
Itching, Burning, Tears
Eye Pain
Itching, Burning, Tears
Lubricant
Red, Itching Eyes

Uses

• For the temporary relief of burning and irritation due to dryness of the eye.
• For the temporary relief of discomfort due to minor irritations of the eye or to exposure to wind or sun.

Warning

Do not Use* If solution changes color or becomes cloudy.

When using this product* To avoid contamination, do not touch tip of container to any surface. Replace cap after using.

Stop use and ask a doctor*If you experience eye pain *If changes in vision *If continued redness or irritation of the eye *If condition worsens or persists for more than 72 hours

If pregnant or breast-feeding, ask a health professional before use.

Keep out of reach of children

Directions

Instill 1 or 2 drops in the affected eye(s) as needed.

Other Information

*Store at room temperature.
*Tamper Evident: Do not use if neckband on bottle is broken or missing

Inactive Ingredients

Alumina Silicata, Calcarea Silicata, Cerium Oxalicum, Distilled Water, Ferrum Muriaticum, Kali Silicatum, Magnesia Muriatica, Magnesia Sulphurica, Natrum Nitricum

Questions or Comments? 1-844-KADESH1

Mon-Fri 9am - 6pm (PST)
www.puriton.us
201, Eonju-ro, Gangnam-gu, Seoul
South Korea 06274

relieves dry eyes, redness
reduces itching burning / pain lubricating